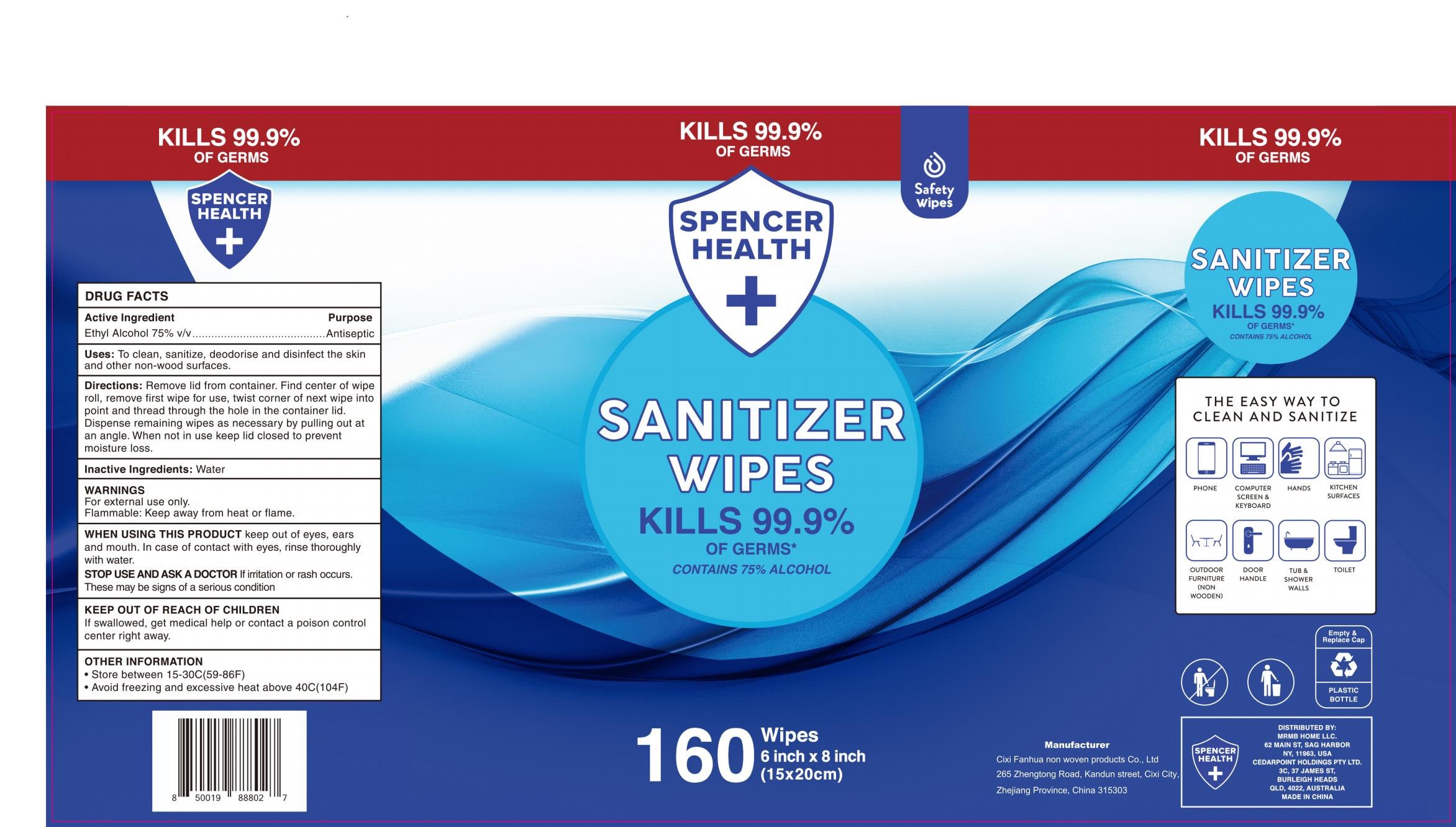 DRUG LABEL: SANITIZER WIPES
NDC: 54826-003 | Form: CLOTH
Manufacturer: Cixi Fanhua Non Woven Products Co., Ltd
Category: otc | Type: HUMAN OTC DRUG LABEL
Date: 20200905

ACTIVE INGREDIENTS: ALCOHOL 597 mL/160 1
INACTIVE INGREDIENTS: WATER

DOSAGE AND ADMINISTRATION

●Store between 15-30°C(59-86°F)
●Avoid freezing and excessive heat above 40°C(104°F)

INACTIVE INGREDIENT

Non-woven fabric

pure water

Quaternary Ammonium Salt

INDICATIONS AND USAGE

Remove lid from container, Find center of wipe roll, remove first wipe for use, twist corner of next wipe into point and thread through the hole in the container lid.Dispense remaining wipes as necessary by pulling out at an angle. When not in use keep lid closed to prevent moisture loss.

ACTIVE INGREDIENT

alcohol

keep out of reach of children

PURPOSE

Disinfection
Sterilization
No Rinseing

WARNINGS

Flammable. Keep away from fire or flame.For external use only.When using this product do not use in or near the eyes. In case of contact, rinse eyes thoroughly with water.Stop use and ask a doctor if iritation or rash appears and lasts.Keep out of reach of children. If swallowed, get medical help right away.